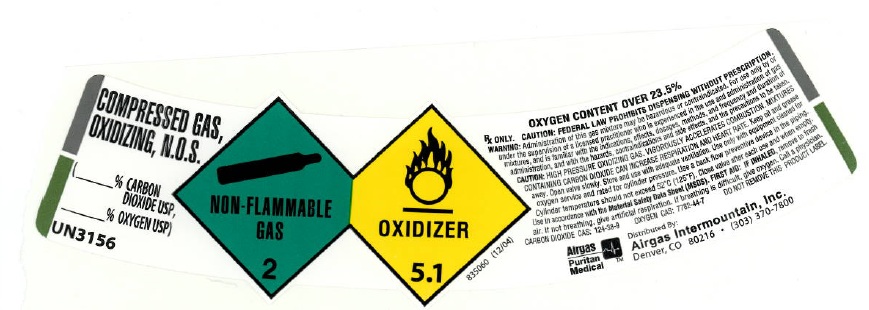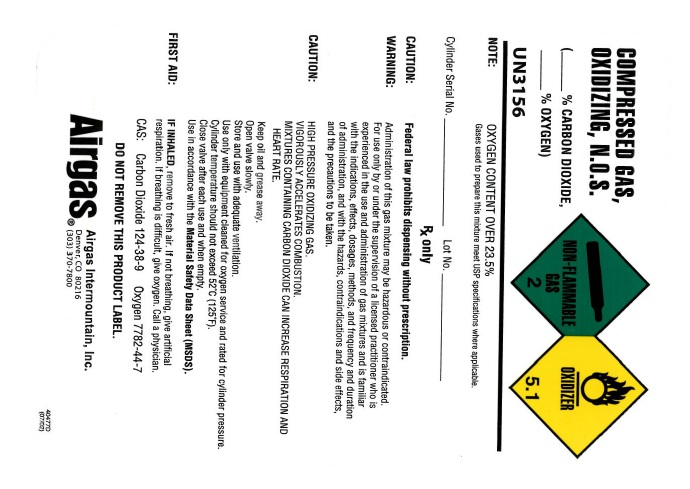 DRUG LABEL: Carbon Dioxide Oxygen Mixture
NDC: 58420-009 | Form: GAS
Manufacturer: Airgas Intermountain Inc
Category: prescription | Type: HUMAN PRESCRIPTION DRUG LABEL
Date: 20101220

ACTIVE INGREDIENTS: Carbon Dioxide 300 mL/1 L; Oxygen 700 mL/1 L

carbon dioxide oxygen mixture

PACKAGE LABEL

COMPRESSED GAS, OXIDIZING N.O.S.
(% CARBON DIOXIDE USP, % OXYGEN USP)
UN3156
NON-FLAMMABLE 2 OXIDIZER 5.1
835060 (12/04)
OXYGEN CONTENT OVER 23.5%
Rx only. CAUTION: Federal law prohibits dispensing without a prescription. WARNING: Administration of this gas mixture may be hazardous or contraindicated. For use only by or under the supervision of a licensed practitioner who is experienced in the use and administration of gas mixtures, and is familiar with the indications, effects, dosages, methods, and frequency and duration of administration, and with the hazards, contraindications and side effects, and the precautions to be taken.
CAUTION: HIGH PRESSURE OXIDIZING GAS. VIGOROUSLY ACCELERATES COMBUSTION. MIXTURES CONTAINING CARBON DIOXIDE CAN INCREASE RESPIRATION AND HEART RATE. Keep oil and grease away. Open valve slowly. Store and use with adequate ventilation. Use only with equipment cleaned for oxygen service and rated for cylinder pressure. Use a back flow preventive device in the piping. Cylinder temperature should not exceed 52oC(125oF). Close valve after each use and when empty. Use in accordance with the Material Safety Data Sheet (MSDS).
FIRST AID: IF INHALED, remove to fresh air. If not breathing, give artificial respiration. If breathing is difficult, give oxygen. Call a physician. CARBON DIOXIDE CAS: 124-38-9 OXYGEN CAS: 7782-44-7
DO NOT REMOVE THIS PRODUCT LABEL.
AIRGAS PURITAN MEDICAL Distributed By: Airgas Intermountain, Inc. Denver, CO 80216 (303) 370-7800

PACKAGE LABEL

COMPRESSED GAS, OXIDIZING N.O.S.
(% CARBON DIOXIDE USP, % OXYGEN USP)
UN3156
NON-FLAMMABLE 2 OXIDIZER 5.1
NOTE: OXYGEN CONTENT OVER 23.5% Gases used to prepare this mixture meet USP specifications where applicable.
Cylinder Serial No. Lot No.
Rx only. CAUTION: Federal law prohibits dispensing without a prescription. WARNING: Administration of this gas mixture may be hazardous or contraindicated. For use only by or under the supervision of a licensed practitioner who is experienced in the use and administration of gas mixtures, and is familiar with the indications, effects, dosages, methods, and frequency and duration of administration, and with the hazards, contraindications and side effects, and the precautions to be taken.
CAUTION: HIGH PRESSURE OXIDIZING GAS. VIGOROUSLY ACCELERATES COMBUSTION. MIXTURES CONTAINING CARBON DIOXIDE CAN INCREASE RESPIRATION AND HEART RATE. Keep oil and grease away. Open valve slowly. Store and use with adequate ventilation. Use only with equipment cleaned for oxygen service and rated for cylinder pressure. Cylinder temperature should not exceed 52oC(125oF). Close valve after each use and when empty. Use in accordance with the Material Safety Data Sheet (MSDS).
FIRST AID: IF INHALED, remove to fresh air. If not breathing, give artificial respiration. If breathing is difficult, give oxygen. Call a physician. CARBON DIOXIDE CAS: 124-38-9 OXYGEN CAS: 7782-44-7
DO NOT REMOVE THIS PRODUCT LABEL.
AIRGAS PURITAN MEDICAL Distributed By: Airgas Intermountain, Inc. Denver, CO 80216 (303) 370-7800
404770 (07/02)